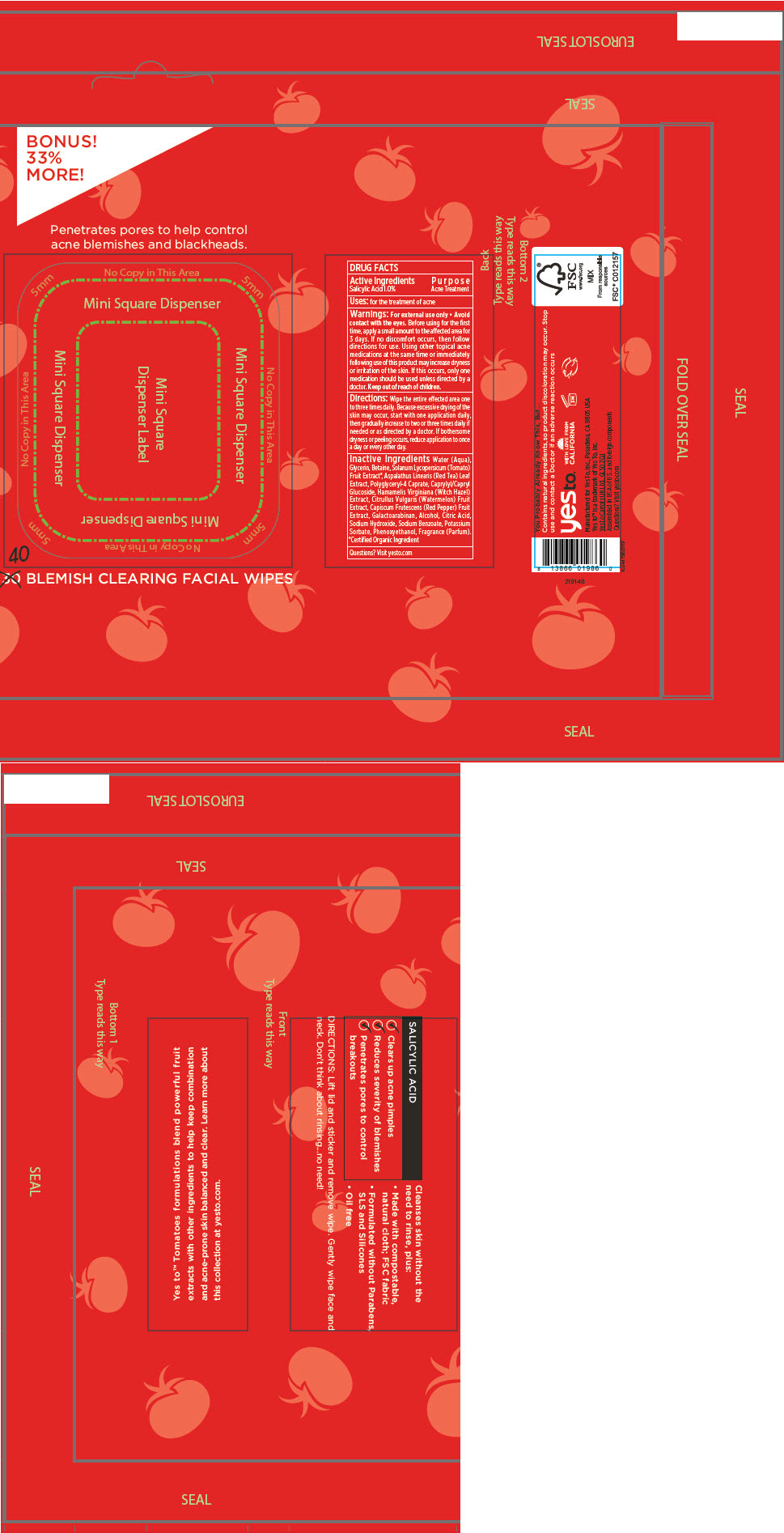 DRUG LABEL: Blemish Clearing Facial Wipes
NDC: 69840-001 | Form: CLOTH
Manufacturer: Yes To Inc.
Category: otc | Type: HUMAN OTC DRUG LABEL
Date: 20210827

ACTIVE INGREDIENTS: Salicylic Acid 10 mg/1 1
INACTIVE INGREDIENTS: WATER; GLYCERIN; BETAINE; CAPRYLYL/CAPRYL OLIGOGLUCOSIDE; TOMATO; WATERMELON; HAMAMELIS VIRGINIANA TOP; CAPSICUM; ASPALATHUS LINEARIS LEAF; GALACTOARABINAN; ALCOHOL; CITRIC ACID MONOHYDRATE; SODIUM HYDROXIDE; SODIUM BENZOATE; POTASSIUM SORBATE; PHENOXYETHANOL; POLYGLYCERYL-4 CAPRATE

Blemish Clearing Facial Wipes

DRUG FACTS

Active Ingredients

Salicylic Acid 1.0%

Purpose

Acne Treatment

Uses

for the treatment of acne

Warnings

For external use only

WHEN USING

- Avoid contact with the eyes.

Before using for the first time, apply a small amount to the affected area for 3 days. If no discomfort occurs, then follow directions for use. Using other topical acne medications at the same time or immediately following use of this product may increase dryness or irritation of the skin. If this occurs, only one medication should be used unless directed by a doctor.

Keep out of reach of children.

Directions

Wipe the entire effected area one to three times daily. Because excessive drying of the skin may occur, start with one application daily, then gradually increase to two or three times daily if needed or as directed by a doctor. If bothersome dryness or peeling occurs, reduce application to once a day or every other day.

Inactive Ingredients

Water (Aqua), Glycerin, Betaine, Solanum Lycopersicum (Tomato) Fruit Extract [Certiﬁed Organic Ingredient] , Aspalathus Linearis (Red Tea) Leaf Extract, Polyglyceryl-4 Caprate, Caprylyl/Capryl Glucoside, Hamamelis Virginiana (Witch Hazel) Extract, Citrullus Vulgaris (Watermelon) Fruit Extract, Capiscum Frutescens (Red Pepper) Fruit Extract, Galactoarabinan, Alcohol, Citric Acid, Sodium Hydroxide, Sodium Benzoate, Potassium Sorbate, Phenoxyethanol, Fragrance (Parfum).

Questions?

Visit yesto.com

PRINCIPAL DISPLAY PANEL - 40 Wipe Packet

BONUS!
33%
MORE!

Penetrates pores to help control
acne blemishes and blackheads.

40 BLEMISH CLEARING FACIAL WIPES